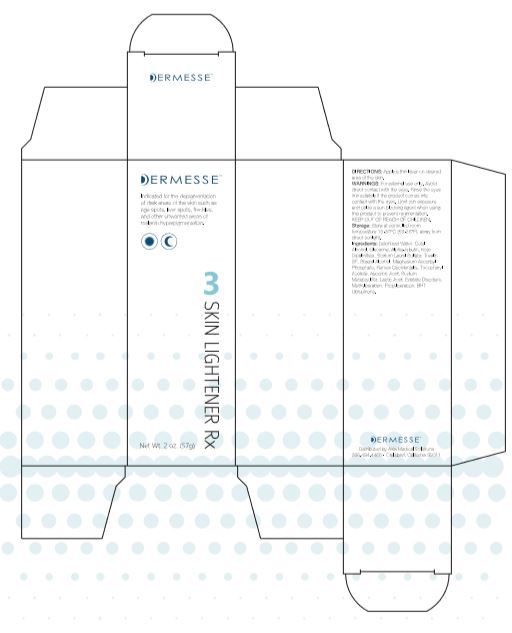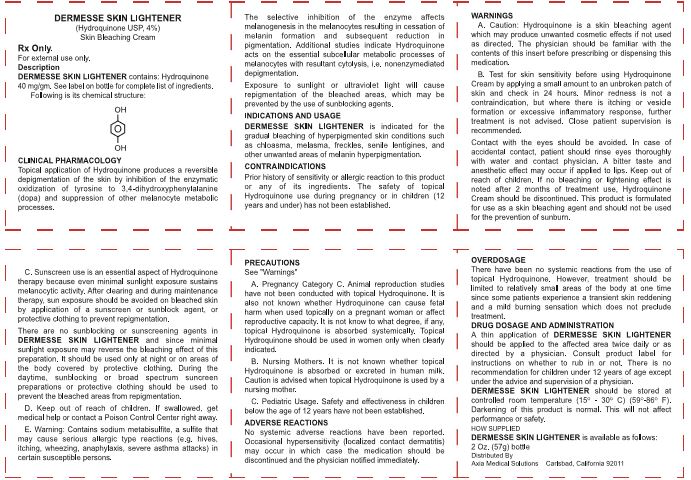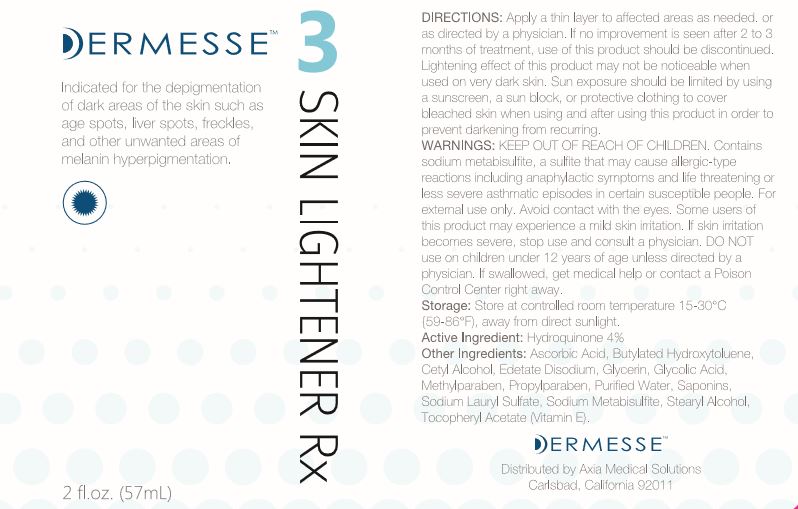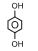 DRUG LABEL: Skin Lightener
NDC: 68723-142 | Form: CREAM
Manufacturer: Axia Medical Solutions, LLC
Category: prescription | Type: HUMAN PRESCRIPTION DRUG LABEL
Date: 20210219

ACTIVE INGREDIENTS: Hydroquinone 40 mg/1 g
INACTIVE INGREDIENTS: ASCORBIC ACID; BUTYLATED HYDROXYTOLUENE; CETYL ALCOHOL; EDETATE DISODIUM; GLYCERIN; GLYCOLIC ACID; METHYLPARABEN; PROPYLPARABEN; WATER; CAULOSIDE D; SODIUM LAURYL SULFATE; SODIUM METABISULFITE; STEARYL ALCOHOL; .ALPHA.-TOCOPHEROL SUCCINATE, D-

Dermesse Skin Lightener

RX Only

FOR EXTERNAL USE ONLY

DESCRIPTION

DERMESSE SKIN LIGHTENER contains: Hydroquinone 40mg/gm. See label on bottle for complete list of ingredients. Following is its chemical structure:

CLINICAL PHARMACOLOGY

Topical application of hydroquinone produces a reversible depigmentation of the skin by inhibition of the enzymatic hydroquinone. oxidation of tyrosine to 3, 4-dihydroxyphenylalanine (dopa) and suppression of other melanocyte metabolic processes.

The selective inhibition of the enzyme affects melanogenesis in the melanocytes resulting in cessation of melanin formation and subsequent reduction in pigmentation. Additional studies indicate Hydroquinone acts on the essential subcellular metabolic processes of melanocytes with resultant cytolysis, i.e. nonenzymediated depigmentation.

Exposure to sunlight or ultraviolet light will cause regimentation of the bleached areas, which may be prevented by the use of sunblocking agents.

INDICATIONS AND USAGE

DERMESSE SKIN LIGHTENER is indicated for the gradual bleaching of hyperpigmented skin conditions such as chlosma, melasma, freckles, senile lentigines and other unwanted areas of melanin hyperpigmentation.

CONTRAINDICATIONS

Prior history of sensitivity or allergic reaction to this product or any of its ingredients. The safety of topical Hydroquinone use during pregnancy or in children (12 years and under) has not been established.

WARNINGS

1. CAUTION: Hydroquinone is a skin bleaching agent which may produce unwanted cosmetic effects if not used as directed. The physician should be familiar with the contents of this insert before prescribing or dispensing this medication.
2. Test for skin sensitivity before using Hydroquinone Cream by applying a small amount to an unbroken patch of skin and check within 24 hours. Minor redness is not a contraindication, but where there is itching and vesicle formation or excessive inflammatory response, further treatment is not advised. Close patient supervision is recommended. Contact with the eyes should be avoided. In case of accidental contact, patient should rinse eyes thoroughly with water and contact physician. A bitter taste and anesthetic effect may occur if applied to lips. Keep out of reach of children. If no bleaching or lightening effect is noted after 2 months of treatment use, Hydroquinone Cream should be discontinued. This product is formulated for use as a skin bleaching agent and should not be used for the prevention of sunburn.
3. Sunscreen use is an essential aspect of Hydroquinone therapy because even minimal sunlight sustains melanocytic activity. After clearing and during maintenance therapy, sun exposure should be avoided on bleached skin by application of a sunscreen or sunblock agent, or protective clothing to prevent repigmentation. There are no sunblocking or sunscreening agents in DERMESSE SKIN LIGHTENER and since minimal sunlight exposure may reverse the bleaching effect of this preparation. It should be used only at night or on areas of the body covered by protective clothing. During the daytime, sunblocking or broad spectrum sunscreen preparations or protective clothing should be used to prevent the bleached areas from repigmentation.
4. Keep out of reach of children. If swallowed, get medical help or contact a Poison Control Center right away.
5. Warning: Contains sodium metabisulfite, a sulfite that may cause serious allergic type reactions (e.g., hives, itching, wheezing, anaphylaxis, severe asthma attack) in certain susceptible persons.

PRECAUTIONS

See Warnings

A. Pregnancy Category C

Animal reproduction studies have not been conducted with topical Hydroquinone. It is also not known whether Hydroquinone can cause fetal harm when used topically on a pregnant woman or can affect reproductive capacity. It is not known to what degree, if any, topical Hydroquinone is absorbed systemically. Topical Hydroquinone should be used in women only when clearly indicated.

B. Nursing mothers

It is not known whether topical Hydroquinone is absorbed or excreted in human milk. Caution is advised when topical Hydroquinone is used by a nursing mother.

C. Pediatric usage

Safety and effectiveness in children below the age of 12 years have not been established.

ADVERSE REACTIONS

No systemic reactions have been reported. Occasional cutaneous hypersensitivity (localized contact dermatitis) may occur in which case the medication should be discontinued and the physician notified immediately

OVERDOSAGE

There have been no systemic reactions reported from the use of topical Hydroquinone. However, treatment should be limited to relatively small areas of the body at one time since some patients experience a transient skin reddening and a mild burning sensation which does not preclude treatment.

DRUG DOSAGE AND ADMINSTRATION

A thin application of DERMESSE SKIN LIGHTENER should be applied to the affected area twice daily or as directed by a physician. Consult product label for instructions on whether to rub in or not. There is no recommendation for children under the age of 12 years of age except under the advice and supervision of a physician.

HOW SUPPLIED

DERMESSE SKIN LIGHTENER is available as follows:

2 Oz. (57g) bottle

STORAGE AND HANDLING

DERMESSE SKIN LIGHTENER should be stored at controlled room temperature (15°-30°C) (59°-86°F). Darkening of this product is normal. This will not affect performance or safety.

Distributed By

Axia Medical Solutions Carlsbad, California 92011